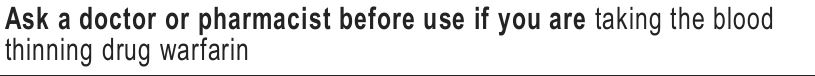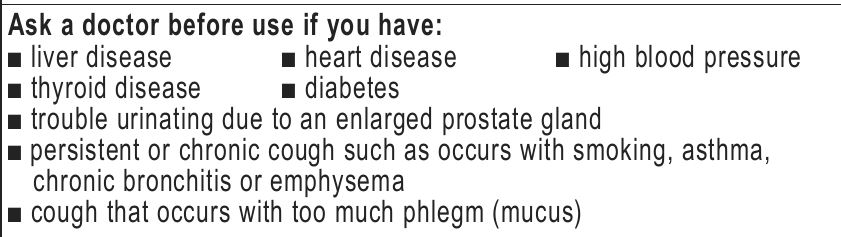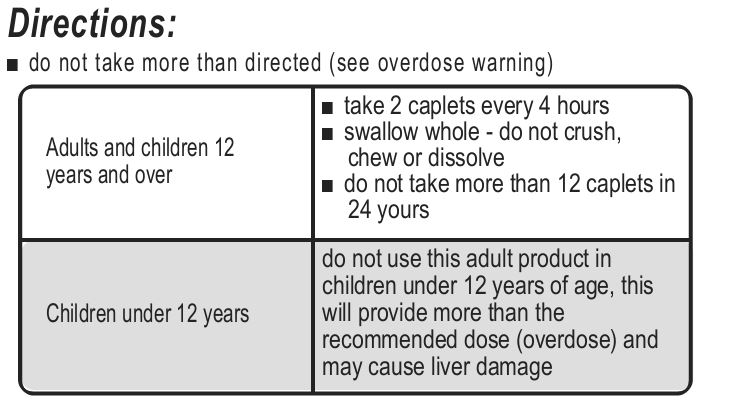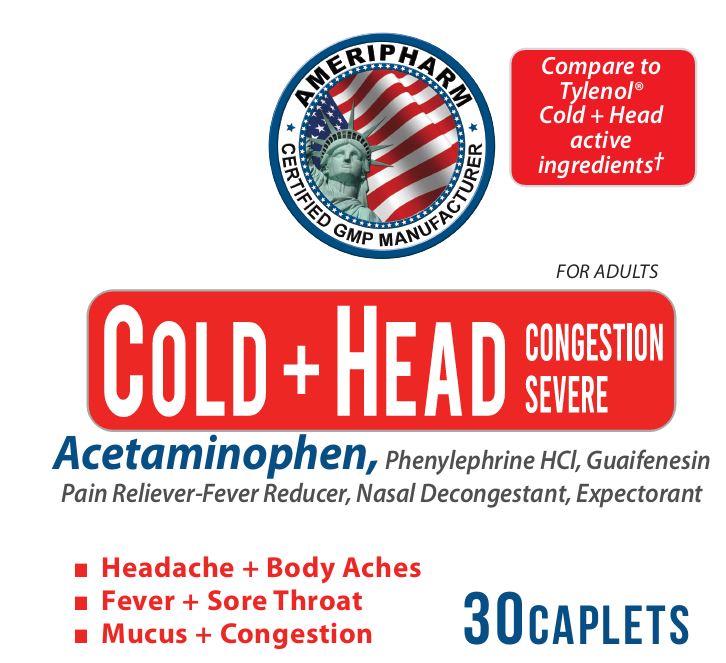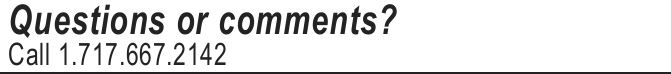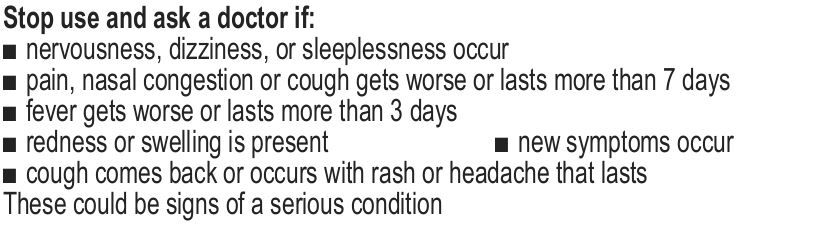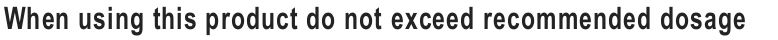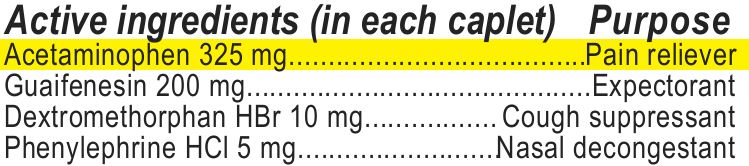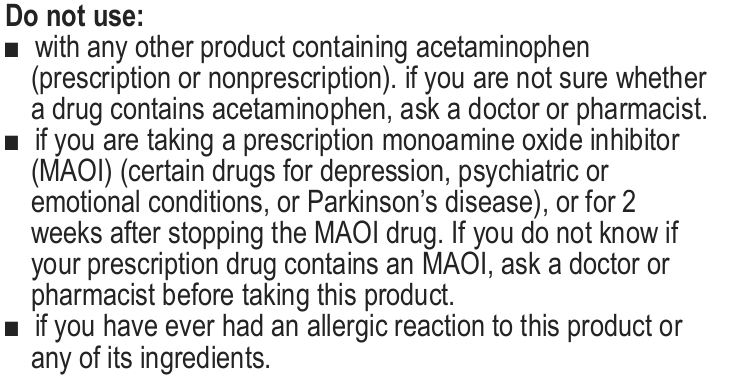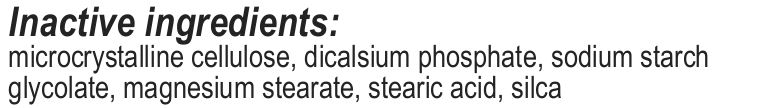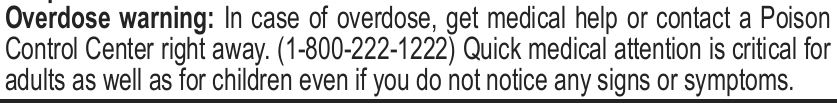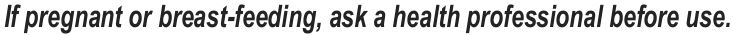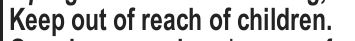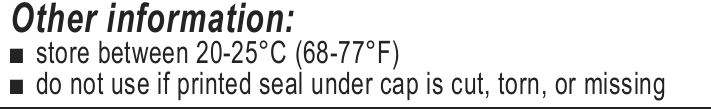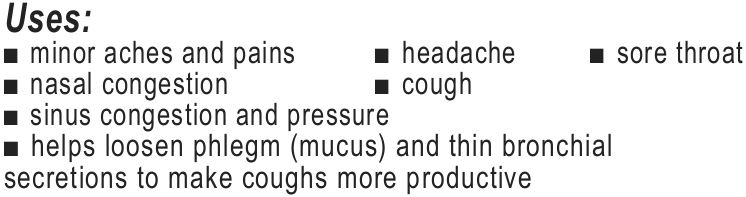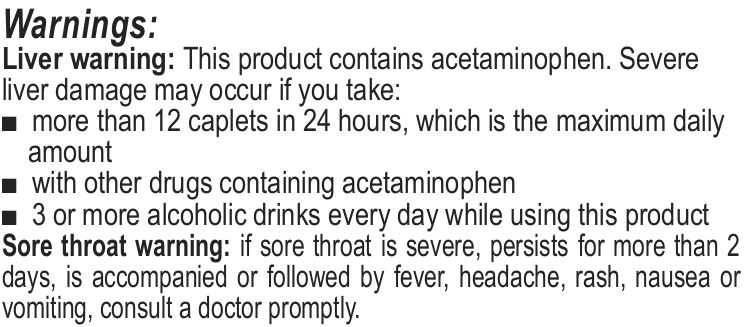 DRUG LABEL: Head and Cold
NDC: 69732-003 | Form: TABLET
Manufacturer: Hi-Tech Nutraceuticals, LLC
Category: otc | Type: HUMAN OTC DRUG LABEL
Date: 20221231

ACTIVE INGREDIENTS: ACETAMINOPHEN 325 mg/1 1; PHENYLEPHRINE HYDROCHLORIDE 5 mg/1 1; DEXTROMETHORPHAN HYDROBROMIDE 10 mg/1 1; GUAIFENESIN 200 mg/1 1
INACTIVE INGREDIENTS: MAGNESIUM STEARATE; SILICON DIOXIDE; CALCIUM PHOSPHATE, DIBASIC, ANHYDROUS; STEARIC ACID; SODIUM STARCH GLYCOLATE TYPE A; MICROCRYSTALLINE CELLULOSE

Head and Cold